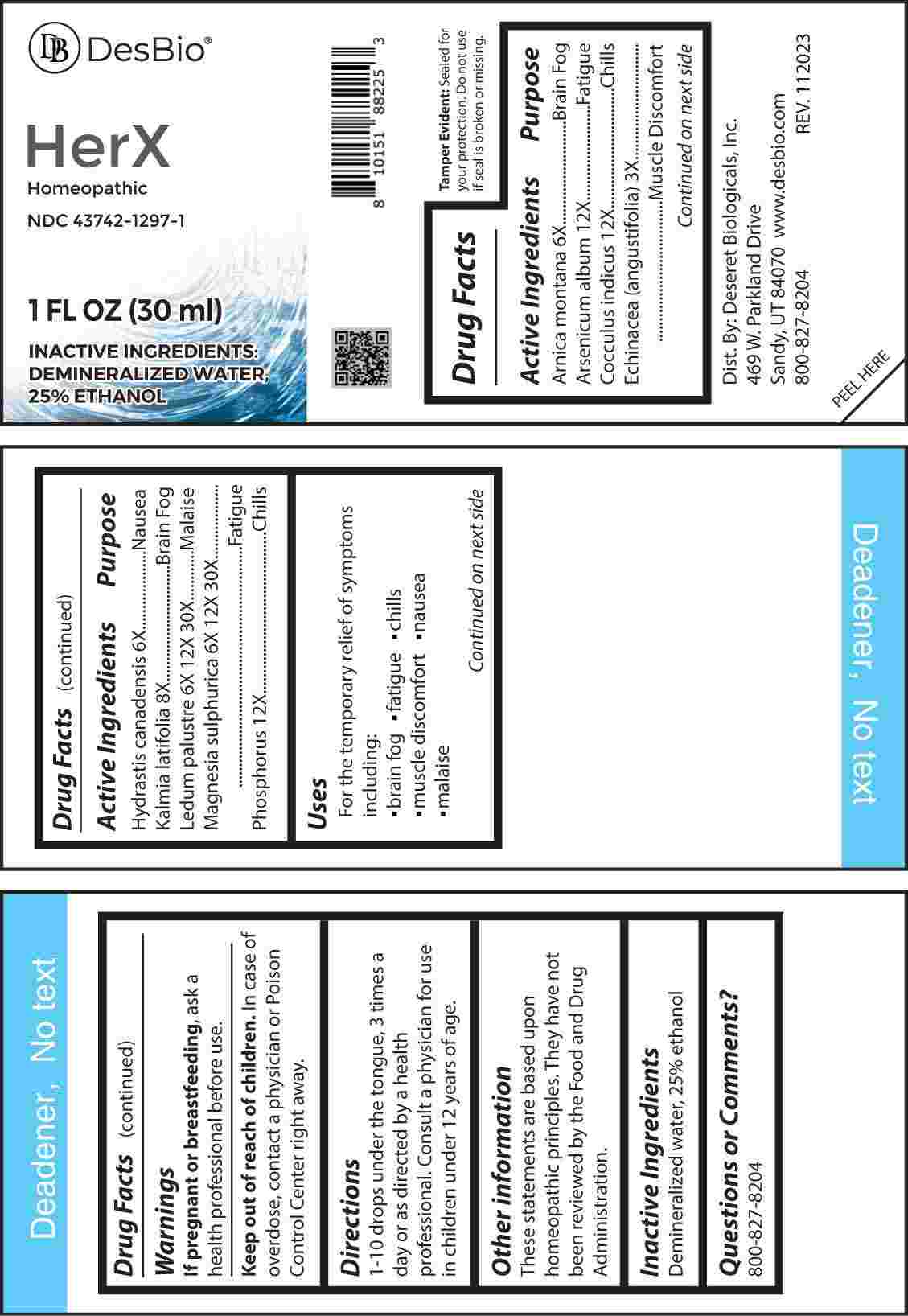 DRUG LABEL: HerX
NDC: 43742-1297 | Form: LIQUID
Manufacturer: Deseret Biologicals, Inc
Category: homeopathic | Type: HUMAN OTC DRUG LABEL
Date: 20240311

ACTIVE INGREDIENTS: ECHINACEA ANGUSTIFOLIA WHOLE 3 [hp_X]/1 mL; ARNICA MONTANA WHOLE 6 [hp_X]/1 mL; GOLDENSEAL 6 [hp_X]/1 mL; RHODODENDRON TOMENTOSUM LEAFY TWIG 6 [hp_X]/1 mL; MAGNESIUM SULFATE HEPTAHYDRATE 6 [hp_X]/1 mL; KALMIA LATIFOLIA LEAF 8 [hp_X]/1 mL; ARSENIC TRIOXIDE 12 [hp_X]/1 mL; ANAMIRTA COCCULUS SEED 12 [hp_X]/1 mL; PHOSPHORUS 12 [hp_X]/1 mL
INACTIVE INGREDIENTS: WATER; ALCOHOL

DRUG FACTS:

ACTIVE INGREDIENTS:

Arnica Montana 6X, Arsenicum Album 12X, Cocculus Indicus 12X, Echinacea (Angustifolia) 3X, Hydrastis Canadensis 6X, Kalmia Latifolia 8X, Ledum Palustre 6X, 12X, 30X, Magnesia Sulphurica 6X, 12X, 30X, Phosphorus 12X.

PURPOSE:

Arnica Montana – Brain Fog, Arsenicum Album - Fatigue, Cocculus Indicus - Chills, Echinacea (Angustifolia) – Muscle Discomfort, Hydrastis Canadensis - Nausea, Kalmia Latifolia – Brain Fog, Ledum Palustre - Malaise, Magnesia Sulphurica - Fatigue, Phosphorus - Chills

USES:

For the temporary relief of symptoms including:

• brain fog • fatigue • chills

• muscle discomfort • nausea

• malaise

These statements are based upon homeopathic principles. They have not been reviewed by the Food and Drug Administration.

WARNINGS:

If pregnant or breast-feeding, ask a health professional before use.

Keep out of reach of children. In case of overdose, contact a physician or Poison Control Center right away.

Tamper Evident: Sealed for your protection. Do not use if seal is broken or missing.

KEEP OUT OF REACH OF CHILDREN:

In case of overdose, contact a physician or Poison Control Center right away.

DIRECTIONS:

1-10 drops under the tongue, 3 times a day or as directed by a health professional. Consult a physician for use in children under 12 years of age.

INACTIVE INGREDIENTS:

Demineralized water, 25% ethanol

QUESTIONS:

Dist. By: Deseret Biologicals, Inc.
469 W. Parkland Drive
Sandy, UT 84070

www.desbio.com

800-827-8204

PACKAGE LABEL DISPLAY:

Des Bio

HerX
Homeopathic
NDC 43742-1297-1

1 FL OZ (30 ml)